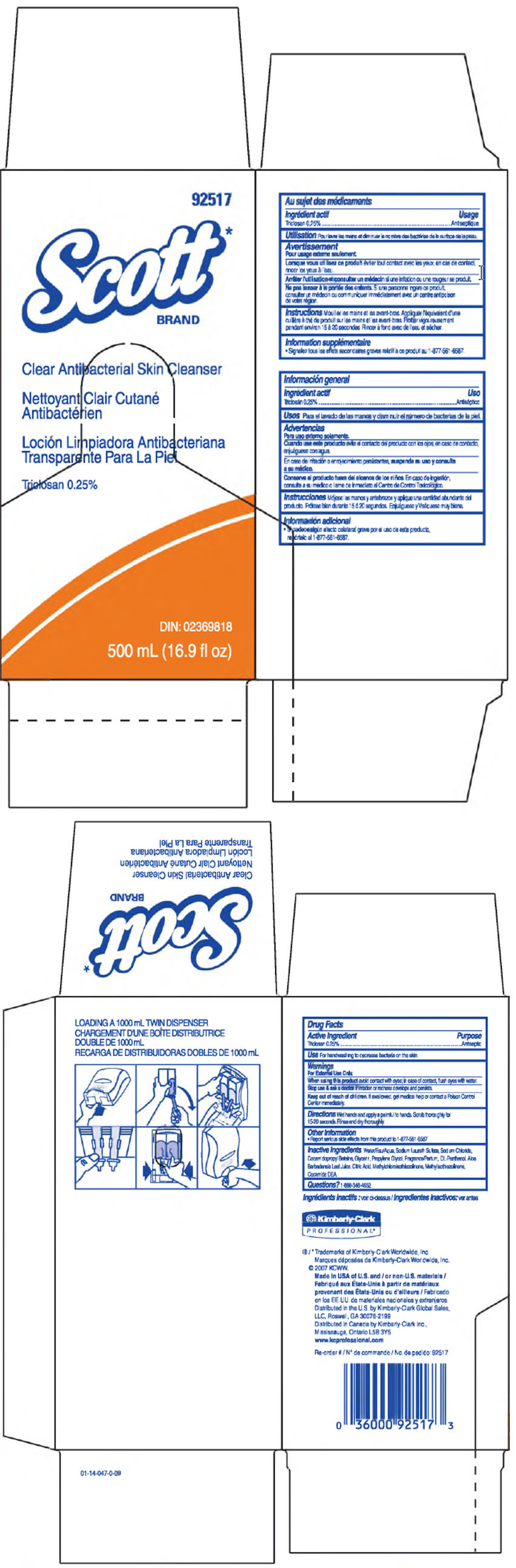 DRUG LABEL: Scott Clear Antibacterial Skin Cleanser
NDC: 55118-205 | Form: SOLUTION
Manufacturer: Kimberly-Clark Corporation
Category: otc | Type: HUMAN OTC DRUG LABEL
Date: 20141007

ACTIVE INGREDIENTS: Triclosan 0.25 g/100 mL
INACTIVE INGREDIENTS: Sodium Laureth-3 Sulfate; Sodium Chloride; Cocamidopropyl Betaine; Coco Diethanolamide; Glycerin; Propylene Glycol; Panthenol; Aloe Vera Leaf; Citric Acid Monohydrate; Methylchloroisothiazolinone; Methylisothiazolinone; Water

Scott Clear Antibacterial Skin Cleanser

Drug Facts

Active Ingredient

Triclosan 0.25%

Purpose

Antiseptic

Use

For handwashing to decrease bacteria on the skin.

Warnings

For External Use Only.

When using this product avoid contact with eyes; in case of contact, flush eyes with water.

STOP USE

Stop use & ask a doctor if irritation or redness develops and persists.

Keep out of reach of children. If swallowed, get medical help or contact a Poison Control Center immediately.

Directions

Wet hands and apply a palmful to hands. Scrub thoroughly for 15-20 seconds. Rinse and dry thoroughly.

Other Information

- Report serious side effects from this product to 1-877-561-6587

Inactive Ingredients

Water, Sodium Laureth Sulfate, Sodium Chloride, Cocamidopropyl Beteine, Glycerin, Propylene Glycol, Frangrance, DL-Panthenol, Aloe Barbadensis Leaf Juice, Citric Acid, Methylchloroisothiazolinone, Methylisothiazolinone, Cocamide DEA.

Questions?

1-888-346-4652

Distributed in the U.S. by Kimberly-Clark Global Sales, LLC, Roswell, GA 30076-2199

Distributed in Canada by Kimberly-Clark Inc., Mississauga, Ontario L5B 3Y5

PRINCIPAL DISPLAY PANEL - 500 mL Carton

92517

Scott*
BRAND

Clear Antibacterial Skin Cleanser

Triclosan 0.25%

DIN: 02369818

500 mL (16.9 fl oz)